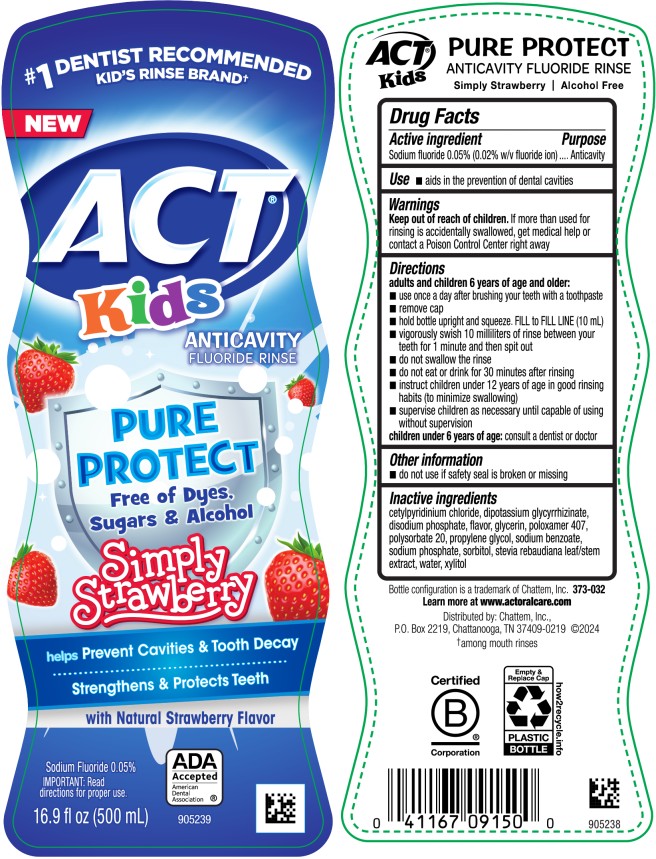 DRUG LABEL: ACT Kids Pure Protect Anticavity- Simply Strawberry
NDC: 41167-0915 | Form: RINSE
Manufacturer: Chattem, Inc.
Category: otc | Type: HUMAN OTC DRUG LABEL
Date: 20260112

ACTIVE INGREDIENTS: SODIUM FLUORIDE 0.5 mg/1 mL
INACTIVE INGREDIENTS: CETYLPYRIDINIUM CHLORIDE; GLYCYRRHIZINATE DIPOTASSIUM; SODIUM PHOSPHATE, DIBASIC, ANHYDROUS; GLYCERIN; POLOXAMER 407; POLYSORBATE 20; PROPYLENE GLYCOL; SODIUM BENZOATE; SODIUM PHOSPHATE; SORBITOL; STEVIA REBAUDIUNA LEAF; WATER; XYLITOL

Act Kids Pure Protect Anticavity Mouthwash Simple Strawberry

ACT Kids Pure Protect Anticavity Mouthwash

Drug Facts

Active ingredients

Sodium fluoride 0.05% (0.02% w/v fluoride ion)

Purpose

Anticavity

Uses

■ aids in the prevention of dental cavities

Warnings

Keep out of reach of children.

If more than used for rinsing is accidentally swallowed, get medical help or contact a Poison Control Center right away.

Directions

adults and children 6 years of age and older:

- use once a day after brushing your teeth with a toothpaste
- remove cap
- hold bottle upright and squeeze. Fill to FILL LINE (10mL)
- vigorously swish 10 milliliters of rinse between your teeth for 1 minute and then spit out
- do not swallow the rinse
- do not eat or drink for 30 minutes after rinsing
- instruct children under 12 years of age in good rinsing habits (to minimize swallowing)
- supervise children as necessary until capable of using without supervision

children under 6 years of age: consult a dentist or doctor

Inactive ingredients

cetylpyridinium chloride, dipotassium glycyrrhizinate, disodium phosphate, flavor, glycerin, poloxamer 407, polysorbate 20, propylene glycol, sodium benzoate, sodium phosphate, sorbitol, stevia rebaudiana leaf/stem extract, water, xylitol

PRINCIPAL DISPLAY PANEL

ACT
Kids
ANTICAVITY
FLUORIDE RINSE
PURE
PROTECT
Free of Dyes,
Sugars & Alcohol
Simply
Strawberry
16.9 fl oz (500 mL)